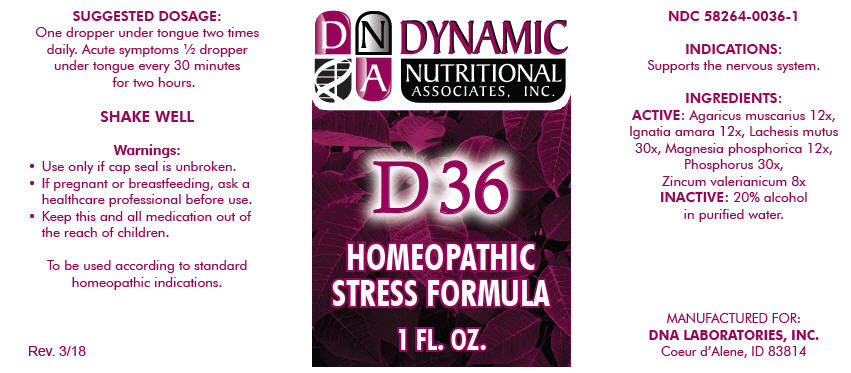 DRUG LABEL: D-36
NDC: 58264-0036 | Form: SOLUTION
Manufacturer: DNA Labs, Inc.
Category: homeopathic | Type: HUMAN OTC DRUG LABEL
Date: 20250113

ACTIVE INGREDIENTS: AMANITA MUSCARIA FRUITING BODY 12 [hp_X]/1 mL; STRYCHNOS IGNATII SEED 12 [hp_X]/1 mL; LACHESIS MUTA VENOM 30 [hp_X]/1 mL; MAGNESIUM PHOSPHATE, DIBASIC TRIHYDRATE 12 [hp_X]/1 mL; PHOSPHORUS 30 [hp_X]/1 mL; ZINC VALERATE DIHYDRATE 8 [hp_X]/1 mL
INACTIVE INGREDIENTS: ALCOHOL; WATER

D-36

NDC 58264-0036-1

INDICATIONS

PURPOSE

Supports the nervous system.

INGREDIENTS

ACTIVE

Agaricus muscarius 12x, Ignatia amara 12x, Lachesis mutus 30x, Magnesia phosphorica 12x, Phosphorus 30x, Zincum valerianicum 8x

INACTIVE

20% alcohol in purified water.

SUGGESTED DOSAGE

One dropper under tongue two times daily. Acute symptoms ½ dropper under tongue every 30 minutes for two hours.

STORAGE AND HANDLING

SHAKE WELL

Warnings

- Use only if cap seal is unbroken.

PREGNANCY OR BREAST FEEDING

- If pregnant or breastfeeding, ask a healthcare professional before use.

KEEP OUT OF REACH OF CHILDREN

- Keep this and all medication out of the reach of children.

To be used according to standard homeopathic indications.

PRINCIPAL DISPLAY PANEL - 1 FL. OZ. Bottle Label

DYNAMIC
NUTRITIONAL
ASSOCIATES, INC.

D 36

HOMEOPATHIC
STRESS FORMULA

1 FL. OZ.